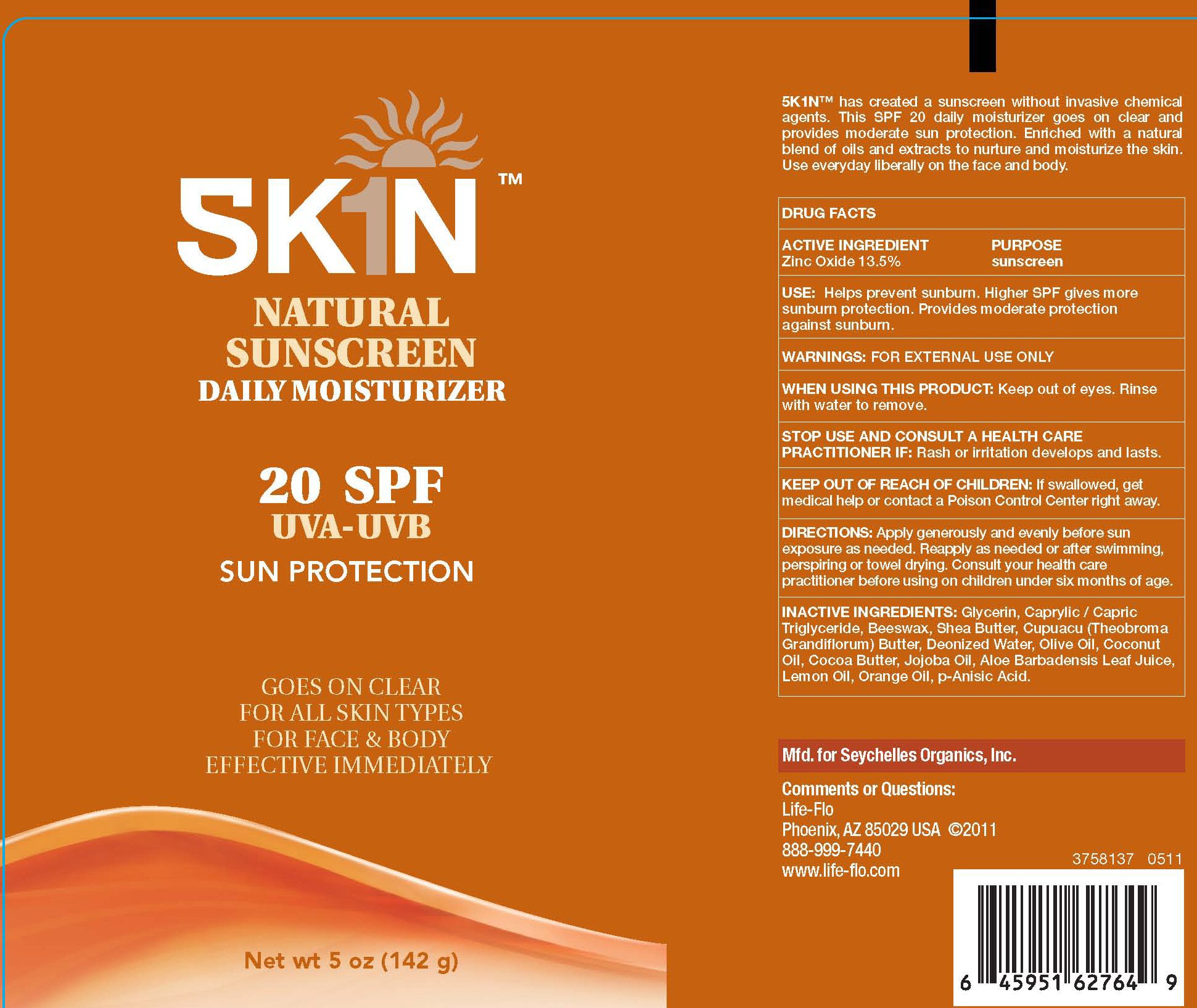 DRUG LABEL: SK1N NATURAL SUNSCREEN SPF 20
NDC: 76245-101 | Form: LOTION
Manufacturer: True Nature Group, Inc.
Category: otc | Type: HUMAN OTC DRUG LABEL
Date: 20110615

ACTIVE INGREDIENTS: ZINC OXIDE 19 g/142 g
INACTIVE INGREDIENTS: GLYCERIN; MEDIUM-CHAIN TRIGLYCERIDES; YELLOW WAX; SHEA BUTTER; THEOBROMA GRANDIFLORUM SEED BUTTER; WATER; OLIVE OIL; COCONUT OIL; COCOA BUTTER; JOJOBA OIL; ALOE VERA LEAF; LEMON OIL; ORANGE OIL; P-ANISIC ACID

SK1N NATURAL SUNSCREEN 20 SPF LABEL

SKIN NATURAL SUNSCREEN TM DAILY MOISTURIZER 20 SPF UVA-UVB SUN PROTECTION

GOES ON CLEAR FOR ALL SKIN TYPES FOR FACES AND BODY EFFECTIVE IMMEDIATELY NET WT 5 OZ (142G)

SK1N TM HAS CREATED A SUNSCREEN WITHOUT INVASIVE CHEMICAL AGENTS. THIS SPF 20 DAILY MOISTURIZER GOES ON CLEAR AND PROVIDES MODERATE SUN PROTECTION. eNRICHED WITH A NATURAL BLEND OF OILS AND EXTRACTS TO NURTURE AND MOISTURIZE THE SKIN. USE EVERYDAY LIBERALLY ON THE FACE AND BODY.

DRUG FACTS ACTIVE INGREDIENT ZINC OXIDE 13.5% PURPOSE SUNSCREEN

USE: HELPS PREVENT SUNBURN. HIGHER SPF GIVES MORE SUNBURN PROTECTION. PROVIDES MODERATE PROTECTION AGAINST SUNBURN.

DIRECTIONS: APPLY GENEROUSLY AND EVENLY BEFORE SUN EXPOSURE AS NEEDED. REAPPLY AS NEEDED OR AFTER SWIMMING, PRESPIRING OR TOWEL DRYING. CONSUKT YOUR HEALTH CARE PRACTITIONER BEFORE USING ON CHILDREN UNDER SIX MONTHS OF AGE.

INACTIVE INGREDIENTS: GLYCERIN, CAPRYLIC/CAPRIC TRIGLYCERIDE, BEESWAX, SHEA BUTTER, CUPUACU (THEOBROMA GRANDIFLORUM) BUTTER, DEONIZED WATER, OLIVE OLI, COCONUT OIL, COCOA BUTTER, JOJOBA OIL, ALOE BARBADENSIS LEAF JUICE, LEMON OIL, ORANGE OIL, P-ANISIC ACID.

MFD. FOR SEYCHELLES ORGANICS, INC. COMMENTS OR QUESTIONS: LIFE-FLO PHOENIX, AZ 85029 USA C2011 888-999-7440 WWW.LIFE-FLO.COM 3758137 0511 6 4595162764 9

WARNINGS

WARNING: FOR EXTERNAL USE ONLY
WHEN USING THIS PRODUCT: KEEP OUT OF THE EYES. RINSE WITH WATER TO REMOVE.
STOP USE AND CONSULT A HEALTH CARE PRACTITIONER IF:RASH OR IRRITATION DEVELOPS AND LASTS.
KEEP OUT OF REACH OF CHILDREN: IF SWALLOWED, GET MEDICAL HELP OR CONTACT A POISON CONTROL CENTER RIGHT AWAY.